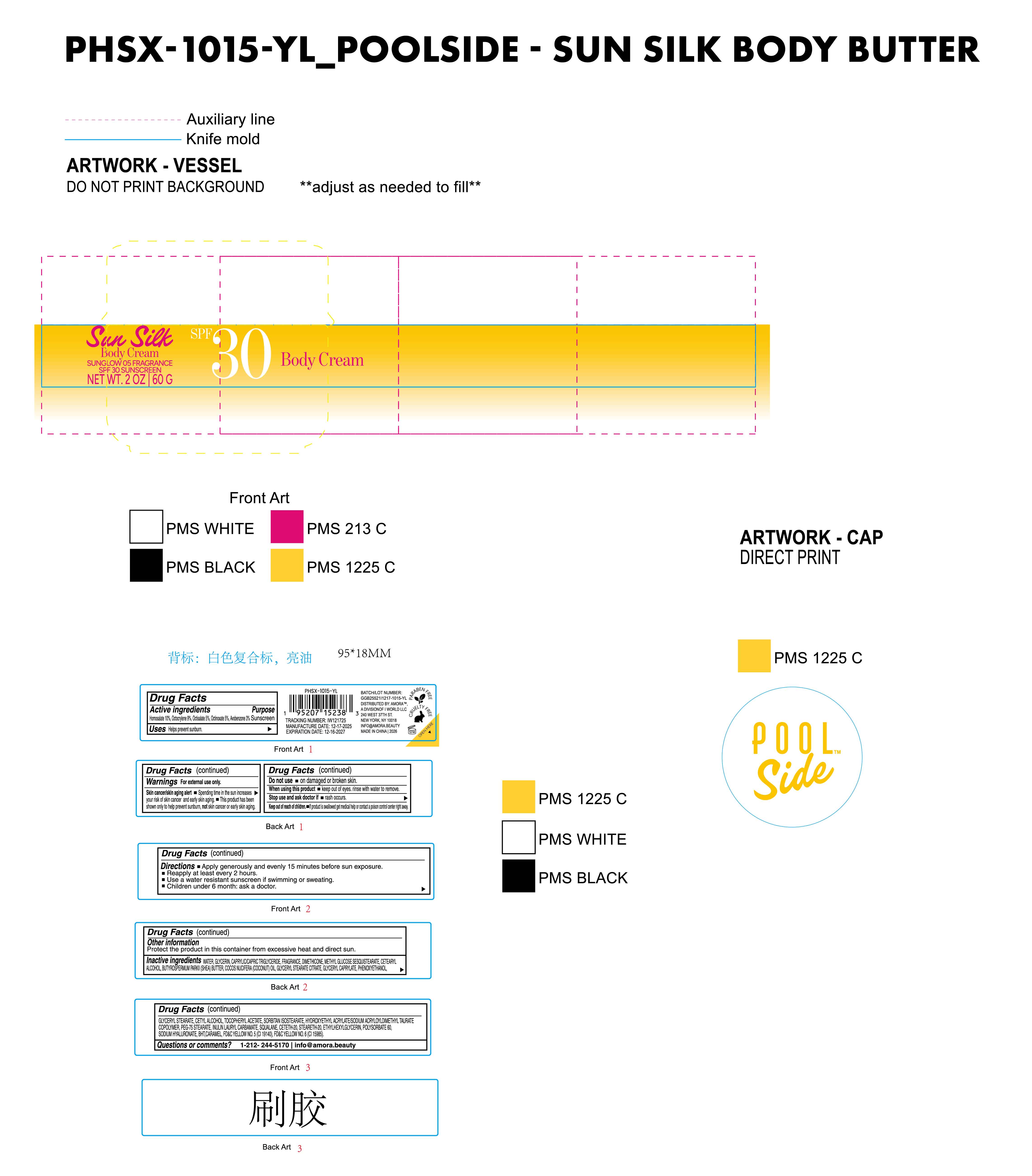 DRUG LABEL: Poolside Sun Silk Body Cream SUNGLOW 05 FRAGRANCE Sunscreen SPF 30 body cream
NDC: 85161-149 | Form: CREAM
Manufacturer: Longway Technology(Guangzhou)Co.,Ltd.
Category: otc | Type: HUMAN OTC DRUG LABEL
Date: 20251204

ACTIVE INGREDIENTS: HOMOSALATE 0.1 g/1 g; OCTISALATE 0.05 g/1 g; OCTOCRYLENE 0.09 g/1 g; OCTINOXATE 0.05 g/1 g; AVOBENZONE 0.03 g/1 g
INACTIVE INGREDIENTS: COCOS NUCIFERA (COCONUT) OIL; DIMETHICONE; FRAGRANCE 13576; METHYL GLUCOSE SESQUISTEARATE; BUTYROSPERMUM PARKII (SHEA) BUTTER; PHENOXYETHANOL; SODIUM HYALURONATE; CI 15985; ALPHA-TOCOPHEROL ACETATE; CAPRYLIC/CAPRIC TRIGLYCERIDE; BHT; STEARETH-20; SQUALANE; CETYL ALCOHOL; GLYCERYL STEARATE CITRATE; GLYCERYL STEARATE; ETHYLHEXYLGLYCERIN; POLYSORBATE 60; CI 19140; CARAMEL; GLYCERIN; CETEARYL ALCOHOL; WATER; PEG-75 STEARATE; INULIN LAURYL CARBAMATE; SORBITAN ISOSTEARATE; HYDROXYETHYL ACRYLATE/SODIUM ACRYLOYLDIMETHYL TAURATE COPOLYMER (100000 MPA.S AT 1.5%); GLYCERYL CAPRYLATE; CETETH-20

ACTIVE INGREDIENT

Homosalate 10%, Octocryene 9%, Octisalate 5% , Octinoxate 5% , Avobenzone 3%

INACTIVE INGREDIENT

WATER, GLYCERIN, CAPRYLIC/CAPRIC TRIGLYCERIDE, FRAGRANCE, DIMETHICONE, METHYL GLUCOSE SESQUISTEARATE, CETEARYL ALCOHOL, BUTYROSPERMUM PARKII (SHEA) BUTTER, COCOS NUCIFERA (COCONUT) OIL, GLYCERYL STEARATE CITRATE, GLYCERYL CAPRYLATE, PHENOXYETHANOL, GLYCERYL STEARATE, CETYL ALCOHOL, TOCOPHERYL ACETATE, SORBITAN ISOSTEARATE, HYDROXYETHYL ACRYLATE/SODIUM ACRYLOYLDIMETHYL TAURATE COPOLYMER, PEG-75 STEARATE, INULIN LAURYL CARBAMATE, SQUALANE, CETETH-20, STEARETH-20, ETHYLHEXYLGLYCERIN, POLYSORBATE 60, SODIUM HYALURONATE, BHT, CARAMEL, FD&C YELLOW NO. 5 (CI 19140), FD&C YELLOW NO. 6 (CI 15985)

Keep out of reach of children.lf product is swallowed get mecical help or contact a poison control center right away.

PURPOSE

Sunscreen

QUESTIONS

1-212-244-5170 info@amora.beauty

OTHER SAFETY INFORMATION

Protect the product in this container from excessive heat and direct sun.

Directions

Apply generously and evenly 15 minutes before sun exposure.
Reapply at least every 2 hours.
Use a water resistant sunscreen if swimming or sweating.
Children under 6 month: ask a doctor.

INDICATIONS AND USAGE

Helps prevent sunburn.

Warnings

For external use only.
Skin cancer/skin aging alert

Spending time in the sun increases your risk of skin cancer and early skin aging.

This product has been shown only to help prevent sunburn, not skin cancer or early skin aging

Do not use on damaged or broken skin.
When using this product keep out of eyes. rinse with water to remove.
Stop use and ask doctor if m rash occurs.
Keep out of reach of children.lf product is swallowed get medical help or contact a poison control center right away.